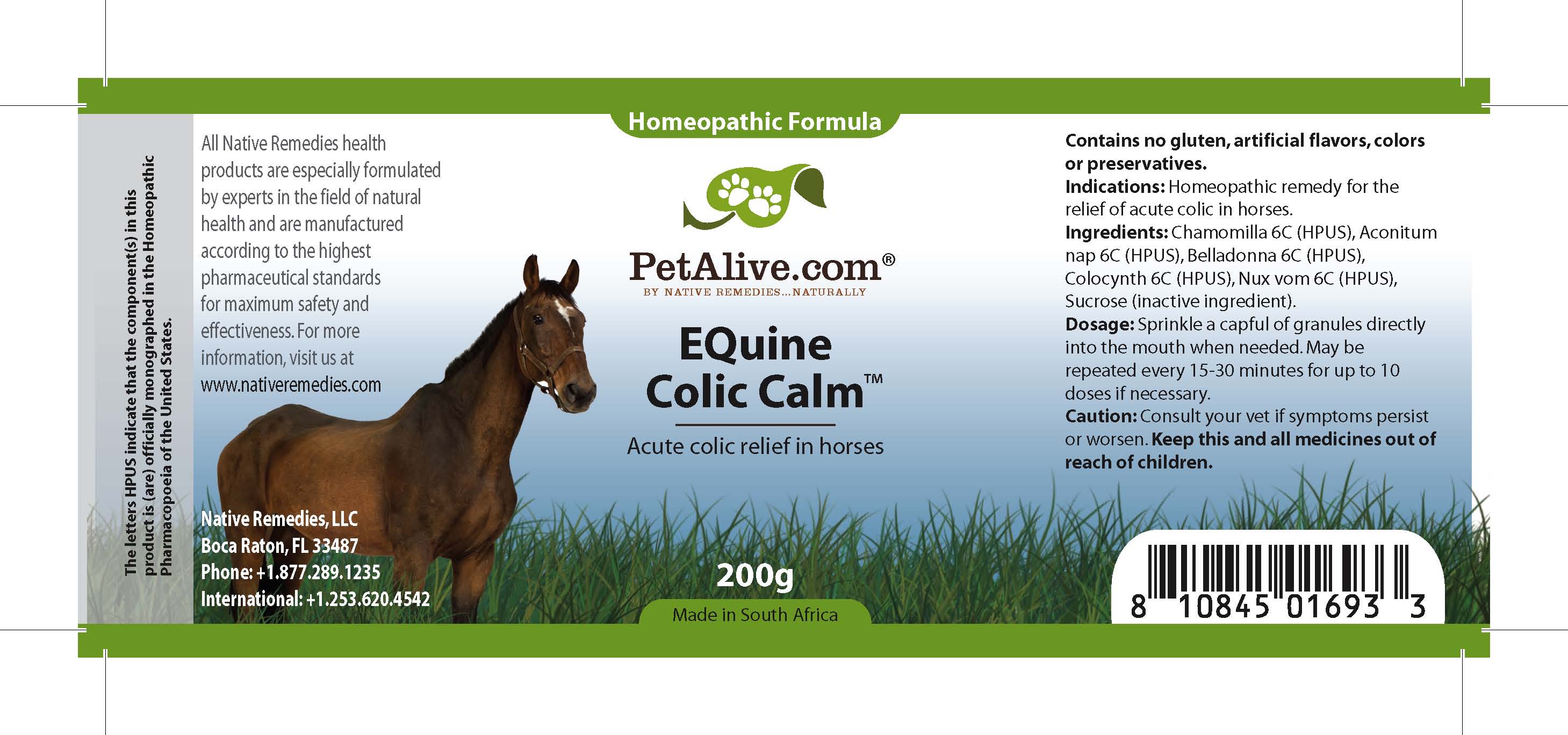 DRUG LABEL: Equine Colic Calm
NDC: 68647-189 | Form: GRANULE
Manufacturer: Feelgood Health
Category: homeopathic | Type: OTC ANIMAL DRUG LABEL
Date: 20100928

ACTIVE INGREDIENTS: MATRICARIA RECUTITA 6 [hp_C]/40 mg; ACONITUM NAPELLUS 6 [hp_C]/40 mg; ATROPA BELLADONNA 6 [hp_C]/40 mg; CITRULLUS COLOCYNTHIS FRUIT PULP 6 [hp_C]/40 mg; STRYCHNOS NUX-VOMICA SEED 6 [hp_C]/40 mg
INACTIVE INGREDIENTS: SUCROSE

EQUINE COLIC CALM

PURPOSE

Promotes digestive and gastrointestinal calm

INDICATIONS AND USAGE

Indications: Homeopathic remedy for the relief of acute colic in horses.

DOSAGE AND ADMINISTRATION

Dosage: Sprinkle a capful of granules directly into the mouth when needed. May be repeated every 15-30 minutes for up to 10 doses if necessary.

GENERAL PRECAUTIONS

Caution: Consult your vet if symptoms persist or worsen. Keep this and all medicines out of reach of children.

ACTIVE INGREDIENT

Ingredients: Chamomilla (6C) (HPUS), Aconitum nap (6C) (HPUS), Belladonna (6C) (HPUS), Colocynth (6C) (HPUS), Nux vom (6C) (HPUS)

Sucrose (inactive ingredient).

WARNINGS

Contains no gluten, artificial flavors, colors or preservatives.

PATIENT COUNSELING INFORMATION

All Native Remedies health products are especially formulated by experts in the field of natural health and are manufactured according to the highest pharmaceutical standards for maximum safety and effectiveness. For more information, visit us at www.petalive.com

Distributed by

Native Remedies, LLC

6531 Park of Commerce Blvd.Suite 160

Boca Raton, FL 33487

Phone: +1.877.289.1235

International: +1.561.999.8857

The letters HPUS indicate that the component(s) in this product is (are) officially monographed in the Homeopathic Pharmacopoeia of the United States.

KEEP OUT OF REACH OF CHILDREN

Keep this and all medicines out of reach of children.